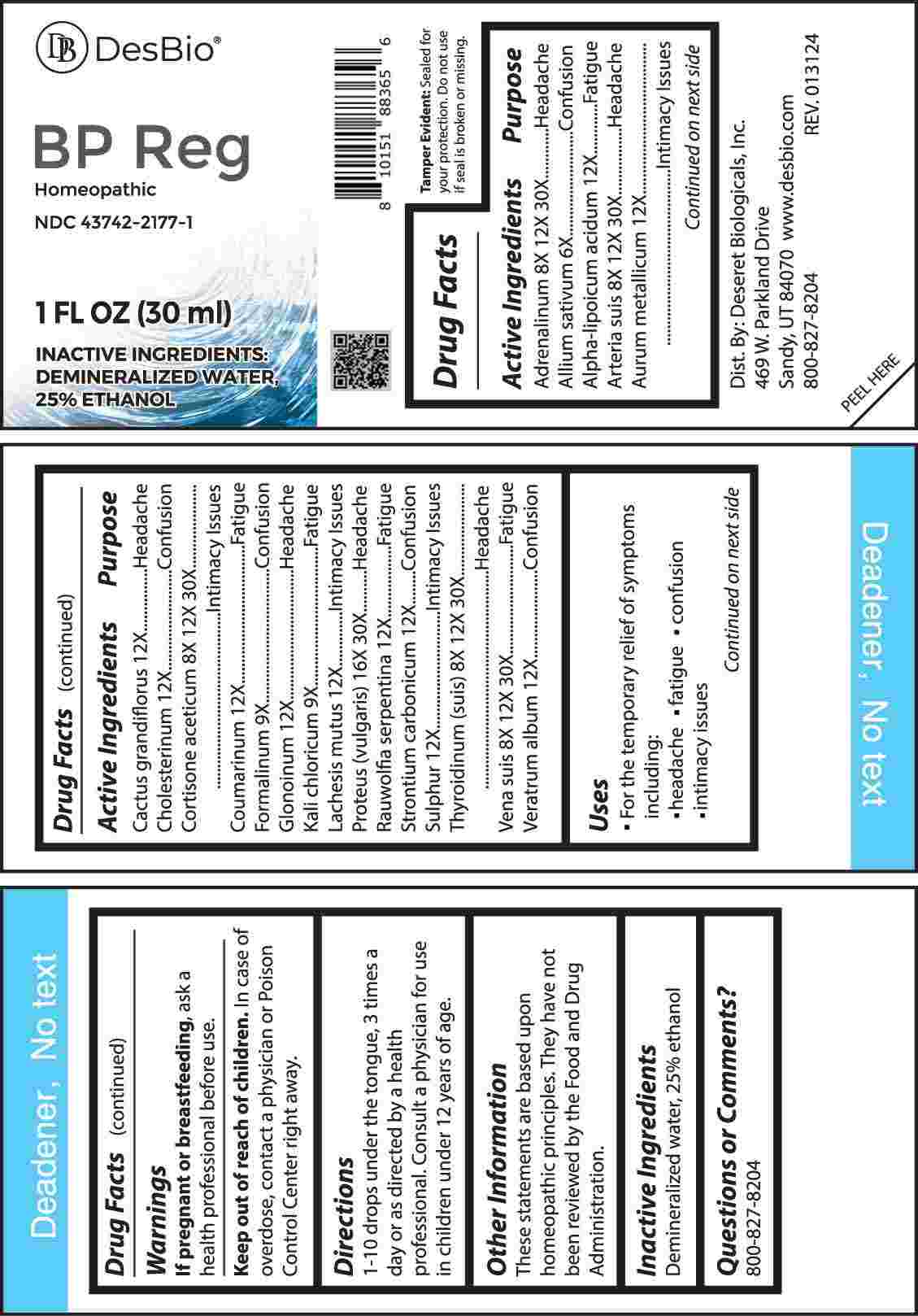 DRUG LABEL: BP Reg
NDC: 43742-2177 | Form: LIQUID
Manufacturer: Deseret Biologicals, Inc.
Category: homeopathic | Type: HUMAN OTC DRUG LABEL
Date: 20240509

ACTIVE INGREDIENTS: EPINEPHRINE 8 [hp_X]/1 mL; GARLIC 6 [hp_X]/1 mL; ALPHA LIPOIC ACID 12 [hp_X]/1 mL; SUS SCROFA ARTERY 8 [hp_X]/1 mL; GOLD 12 [hp_X]/1 mL; SELENICEREUS GRANDIFLORUS STEM 12 [hp_X]/1 mL; CHOLESTEROL 12 [hp_X]/1 mL; CORTISONE ACETATE 8 [hp_X]/1 mL; COUMARIN 12 [hp_X]/1 mL; FORMALDEHYDE SOLUTION 9 [hp_X]/1 mL; NITROGLYCERIN 12 [hp_X]/1 mL; POTASSIUM CHLORATE 9 [hp_X]/1 mL; LACHESIS MUTA VENOM 12 [hp_X]/1 mL; PROTEUS VULGARIS 16 [hp_X]/1 mL; RAUWOLFIA SERPENTINA 12 [hp_X]/1 mL; STRONTIUM CARBONATE 12 [hp_X]/1 mL; SULFUR 12 [hp_X]/1 mL; THYROID 8 [hp_X]/1 mL; SUS SCROFA VEIN 8 [hp_X]/1 mL; VERATRUM ALBUM ROOT 12 [hp_X]/1 mL
INACTIVE INGREDIENTS: WATER; ALCOHOL

DRUG FACTS:

ACTIVE INGREDIENTS:

Adrenalinum 8X, 12X, 30X, Allium Sativum 6X, Alpha-Lipoicum Acidum 12X, Arteria Suis 8X, 12X, 30X, Aurum Metallicum 12X, Cactus Grandiflorus 12X, Cholesterinum 12X, Cortisone Aceticum 8X, 12X, 30X, Coumarinum 12X, Formalinum 9X, Glonoinum 12X, Kali Chloricum 9X, Lachesis Mutus 12X, Proteus (Vulgaris) 16X, 30X, Rauwolfia Serpentina 12X, Strontium Carbonicum 12X, Sulphur 12X, Thyroidinum (Suis) 8X, 12X, 30X, Vena Suis 8X, 12X, 30X, Veratrum Album 12X.

PURPOSE:

Adrenalinum – Headache, Allium Sativum - Confusion, Alpha-Lipoicum Acidum - Fatigue, Arteria Suis - Headache, Aurum Metallicum – Intimacy Issues, Cactus Grandiflorus - Headache, Cholesterinum - Confusion, Cortisone Aceticum – Intimacy Issues, Coumarinum - Fatigue, Formalinum - Confusion, Glonoinum - Headache, Kali Chloricum - Fatigue, Lachesis Mutus – Intimacy Issues, Proteus (Vulgaris) - Headache, Rauwolfia Serpentina - Fatigue, Strontium Carbonicum - Confusion, Sulphur – Intimacy Issues, Thyroidinum (Suis) - Headache, Vena Suis - Fatigue, Veratrum Album - Confusion

USES:

• For the temporary relief of symptoms including:

• headache • fatigue • confusion • intimacy issues

These statements are based upon homeopathic principles. They have not been reviewed by the Food and Drug Administration.

WARNINGS:

If pregnant or breast-feeding, ask a health professional before use.

Keep out of reach of children. In case of overdose, contact a physician or Poison Control Center right away.

Tamper Evident: Sealed for your protection. Do not use if seal is broken or missing.

KEEP OUT OF REACH OF CHILDREN:

In case of overdose, contact a physician or Poison Control Center right away.

DIRECTIONS:

1-10 drops under the tongue, 3 times a day or as directed by a health professional. Consult a physician for use in children under 12 years of age.

INACTIVE INGREDIENTS:

Demineralized water, 25% ethanol

QUESTIONS:

Dist. By: Deseret Biologicals, Inc.

469 W. Parkland Drive

Sandy, UT 84070

www.desbio.com

800-827-8204

PACKAGE LABEL DISPLAY:

DesBio

BP Reg

Homeopathic

NDC 43742-2177-1

1 FL OZ (30 ml)